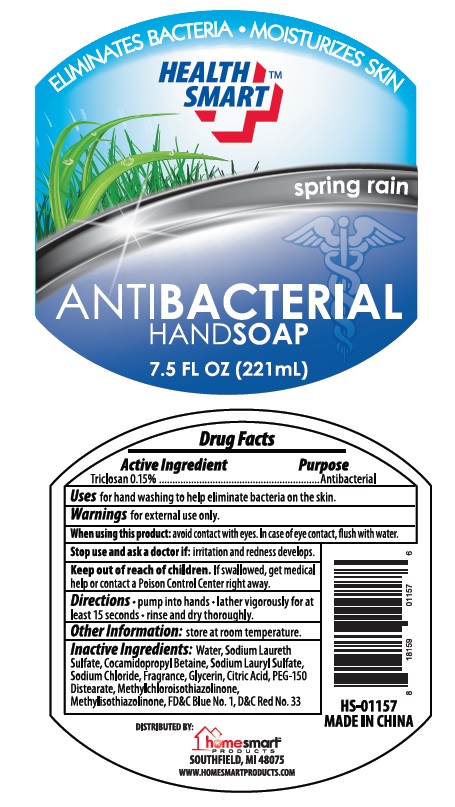 DRUG LABEL: Health Smart Antibacterial Spring Rain
                
NDC: 52862-310 | Form: SOLUTION
Manufacturer: International Wholesale, Inc.
Category: otc | Type: HUMAN OTC DRUG LABEL
Date: 20131224

ACTIVE INGREDIENTS: TRICLOSAN 0.15 mg/100 mL
INACTIVE INGREDIENTS: WATER; SODIUM LAURETH-3 SULFATE; COCAMIDOPROPYL BETAINE; SODIUM LAURYL SULFATE; SODIUM CHLORIDE; GLYCERIN; CITRIC ACID MONOHYDRATE; PEG-150 DISTEARATE; METHYLCHLOROISOTHIAZOLINONE; METHYLISOTHIAZOLINONE; FD&C BLUE NO. 1; D&C RED NO. 33

Antibacterial Hand Soap

Drug Facts

Active Ingredients

Triclosan 0.15%

Purpose

Antibacterial

Uses

for hand washing to help eliminate bacteria on the skin.

Warnings

for external use only.

When using this product avoid contact with eyes. If case of eye contact, flush with water.

Stop use and ask a doctor if: irritation and redness develops.

Keep out of reach of children. If swallowed, get medical help or contact a Poison Control Center right away.

Directions

- pump into hands
- lather vigorously for at least 15 seconds
- rinse and dry thoroughly.

Other information:

store at room temperature.

Inactive ingredients

Water, Sodium Laureth Sulfate, Cocamidopropyl Betaine, Sodium Lauryl Sulfate, Sodium Chloride, Fragrance, Glycerin, Citric Acid, PEG-150 Distearate, Methylchloroisothiazolinone, Methylisothiazolinone, FD&C Blue No. 1, D&C Red No. 33

MADE IN CHINA.

DISTRIBUTED BY:
homesmartTM
PRODUCTS
SOUTHFIELD, MI 48075
WWW.HOMESMARTPRODUCTS.COM

Package Label

ELIMINATES BACTERIA •MOISTURIZES SKIN

HEALTH SMARTTM
spring rain
ANTIBACTERIAL
HAND SOAP
7.5 FL OZ [221 mL]